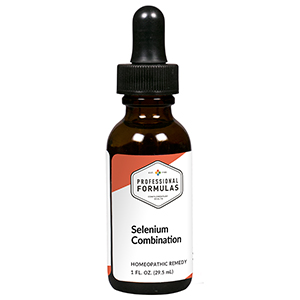 DRUG LABEL: Selenium Combination
NDC: 63083-9245 | Form: LIQUID
Manufacturer: Professional Complementary Health Formulas
Category: homeopathic | Type: HUMAN OTC DRUG LABEL
Date: 20190815

ACTIVE INGREDIENTS: RHODODENDRON TOMENTOSUM LEAFY TWIG 4 [hp_X]/29.5 mL; URTICA URENS WHOLE 4 [hp_X]/29.5 mL; HORSE CHESTNUT 6 [hp_X]/29.5 mL; ARCTIUM LAPPA ROOT OIL 6 [hp_X]/29.5 mL; CALCIUM FLUORIDE 6 [hp_X]/29.5 mL; GALIUM APARINE WHOLE 6 [hp_X]/29.5 mL; STRYCHNOS IGNATII SEED 6 [hp_X]/29.5 mL; PHOSPHORIC ACID 6 [hp_X]/29.5 mL; SULFUR 8 [hp_X]/29.5 mL; THUJA OCCIDENTALIS LEAF 8 [hp_X]/29.5 mL; OXOGLURIC ACID 10 [hp_X]/29.5 mL; FUMARIC ACID 10 [hp_X]/29.5 mL; BEEF KIDNEY 10 [hp_X]/29.5 mL; BEEF LIVER 10 [hp_X]/29.5 mL; SODIUM DIETHYL OXALACETATE 10 [hp_X]/29.5 mL; BOS TAURUS PLACENTA 10 [hp_X]/29.5 mL; SELENIUM 10 [hp_X]/29.5 mL; CHICKEN SKIN, COOKED 10 [hp_X]/29.5 mL; BOS TAURUS SPLEEN 10 [hp_X]/29.5 mL; AMMONIUM Cation 12 [hp_X]/29.5 mL; MERCURIUS SOLUBILIS 13 [hp_X]/29.5 mL; CORTISONE ACETATE 28 [hp_X]/29.5 mL; FORMIC ACID 198 [hp_X]/29.5 mL
INACTIVE INGREDIENTS: ALCOHOL; WATER

R245

ACTIVE INGREDIENTS

Ledum palustre 4X
Urtica urens 4X
Aesculus hippocastanum 6X
Arctium lappa 6X
Calcarea fluorica 6X
Galium aparine 6X
Ignatia amara 6X
Phosphoricum acidum 6X
Sulphur 8X
Thuja occidentalis 8X
a-Ketoglutaricum acidum 10X
Fumaricum acidum 10X
Kidney 10X
Liver 10X
Natrum oxalaceticum 10X
Placenta 10X
Selenium metallicum 10X
Skin 10X
Spleen 10X
Sanguinarinum nitricum 12X
Mercurius solubilis 13X
Cortisone aceticum 28X
Formicum acidum 198X

QUESTIONS

Professional Formulas

PO Box 2034 Lake Oswego, OR 97035

INDICATIONS

For the temporary relief of mild skin inflammation such as eczema, acne, or dermatitis.*

PURPOSE

*Claims based on traditional homeopathic practice, not accepted medical evidence. Not FDA evaluated.

WARNINGS

Consult a doctor if condition worsens or if symptoms persist. Keep out of the reach of children. In case of overdose, get medical help or contact a poison control center right away. If pregnant or breastfeeding, ask a healthcare professional before use.

Keep out of the reach of children.

PREGNANCY OR BREAST FEEDING

If pregnant or breastfeeding, ask a healthcare professional before use.

DIRECTIONS

Place drops under tongue 30 minutes before/after meals. Adults and children 12 years and over: Take 10 drops up to 3 times per day. Consult a physician for use in children under 12 years of age.

OTHER INFORMATION

Tamper resistant. If seal is broken, do not use. After opening, close container tightly and store at room temperature away from heat.

INACTIVE INGREDIENTS

40% ethanol, purified water.

LABEL

Est 1985

Professional Formulas

Complementary Health

Selenium Combination

Homeopathic Remedy

1 FL. OZ. (29.5 mL)